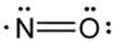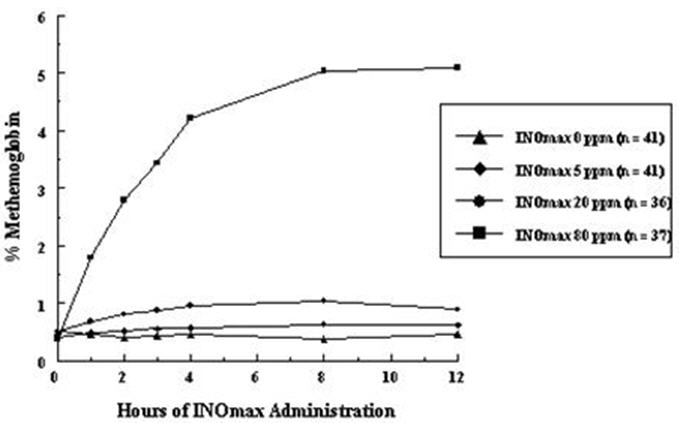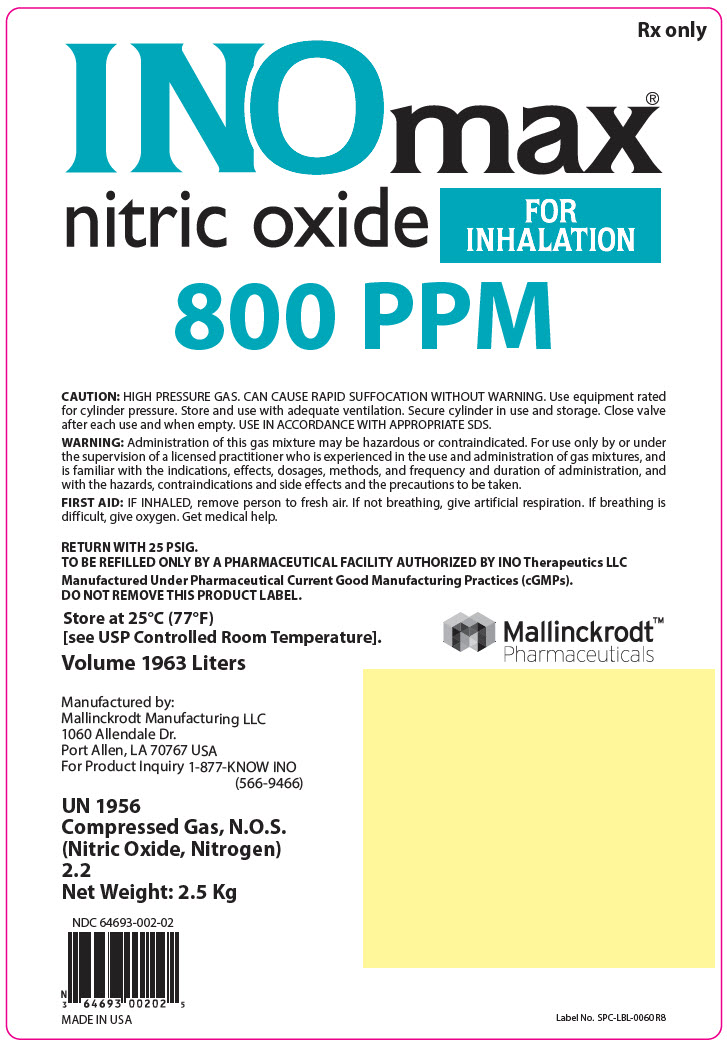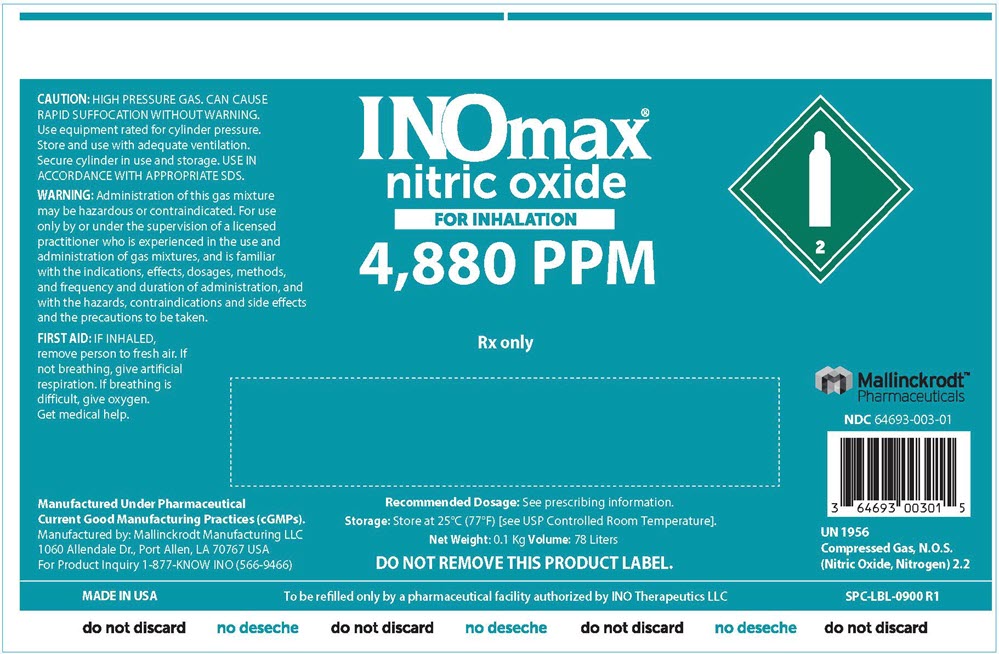 DRUG LABEL: INOMAX
NDC: 64693-002 | Form: GAS
Manufacturer: INO Therapeutics LLC
Category: prescription | Type: HUMAN PRESCRIPTION DRUG LABEL
Date: 20251212

ACTIVE INGREDIENTS: NITRIC OXIDE 0.98 mg/1 L
INACTIVE INGREDIENTS: NITROGEN

HIGHLIGHTS OF PRESCRIBING INFORMATION

These highlights do not include all the information needed to use INOMAX safely and effectively. See full prescribing information for INOMAX.
INOMAX® (nitric oxide) gas, for inhalation
Initial U.S. Approval: 1999

1 INDICATIONS AND USAGE

INOmax is a vasodilator indicated to improve oxygenation and reduce the need for extracorporeal membrane oxygenation in term and near-term (>34 weeks gestation) neonates with hypoxic respiratory failure associated with clinical or echocardiographic evidence of pulmonary hypertension in conjunction with ventilatory support and other appropriate agents.

2 DOSAGE AND ADMINISTRATION

The recommended dose is 20 ppm, maintained for up to 14 days or until the underlying oxygen desaturation has resolved (2.1).

Doses greater than 20 ppm are not recommended (2.1, 5.2)

Administration:

- Avoid abrupt discontinuation (2.2, 5.1).

3 DOSAGE FORMS AND STRENGTHS

INOmax (nitric oxide) is a gas available in 800 and 4,880 ppm concentrations (3).

4 CONTRAINDICATIONS

Neonates dependent on right-to-left shunting of blood (4).

5 WARNINGS AND PRECAUTIONS

Rebound: Abrupt discontinuation of INOmax may lead to worsening oxygenation and increasing pulmonary artery pressure (5.1).

Methemoglobinemia: Methemoglobin increases with the dose of nitric oxide; following discontinuation or reduction of nitric oxide, methemoglobin levels return to baseline over a period of hours (5.2).

Elevated NO2 Levels: Monitor NO2 levels (5.3).

Heart Failure: In patients with pre-existing left ventricular dysfunction, INOmax may increase pulmonary capillary wedge pressure leading to pulmonary edema (5.4).

6 ADVERSE REACTIONS

The most common adverse reaction is hypotension. (6).

To report SUSPECTED ADVERSE REACTIONS, contact INO Therapeutics at 1-877-566-9466 and http://www.inomax.com/ or FDA at 1-800-FDA-1088 or www.fda.gov/medwatch.

7 DRUG INTERACTIONS

Nitric oxide donor compounds may increase the risk of developing methemoglobinemia (7).

FULL PRESCRIBING INFORMATION

1 INDICATIONS AND USAGE

INOmax® is indicated to improve oxygenation and reduce the need for extracorporeal membrane oxygenation in term and near-term (>34 weeks gestation) neonates with hypoxic respiratory failure associated with clinical or echocardiographic evidence of pulmonary hypertension in conjunction with ventilatory support and other appropriate agents.

2 DOSAGE AND ADMINISTRATION

2.1 Dosage

Term and near-term neonates with hypoxic respiratory failure

The recommended dose of INOmax is 20 ppm. Maintain treatment up to 14 days or until the underlying oxygen desaturation has resolved and the neonate is ready to be weaned from INOmax therapy.

Doses greater than 20 ppm are not recommended [see Warnings and Precautions (5.2)].

2.2 Administration

Nitric Oxide Delivery Systems

INOmax must be administered using a calibrated, FDA-cleared Nitric Oxide Delivery System (NODS). There are various FDA-cleared NODS; refer to the NODS labeling to determine which NODS to use with this drug product and for needed information on training and technical support for users of this drug product with the NODS.

When utilizing a nitric oxide delivery system specifically cleared for use in the MRI suite (e.g., the INOmax DSIR® Plus MRI) only use INOmax MR conditional cylinders at 100 gauss or less [see How Supplied/Storage and Handling (16)].

Keep available a backup battery power supply and an independent reserve nitric oxide delivery system to address power and system failures.

Monitoring

Measure methemoglobin within 4-8 hours after initiation of treatment with INOmax and periodically throughout treatment [see Warnings and Precautions (5.2)].

Monitor for PaO2 and inspired NO2 during INOmax administration [see Warnings and Precautions (5.3)].

Weaning and Discontinuation

Avoid abrupt discontinuation of INOmax [see Warnings and Precautions (5.1)]. To wean INOmax, downtitrate in several steps, pausing several hours at each step to monitor for hypoxemia.

3 DOSAGE FORMS AND STRENGTHS

INOmax (nitric oxide) gas is available in 800 and 4,880 ppm concentrations.

4 CONTRAINDICATIONS

INOmax is contraindicated in neonates dependent on right-to-left shunting of blood.

5 WARNINGS AND PRECAUTIONS

5.1 Rebound Pulmonary Hypertension Syndrome following Abrupt Discontinuation

Wean from INOmax [see Dosage and Administration (2.2)]. Abrupt discontinuation of INOmax may lead to worsening oxygenation and increasing pulmonary artery pressure, i.e., Rebound Pulmonary Hypertension Syndrome. Signs and symptoms of Rebound Pulmonary Hypertension Syndrome include hypoxemia, systemic hypotension, bradycardia, and decreased cardiac output. If Rebound Pulmonary Hypertension occurs, reinstate INOmax therapy immediately.

5.2 Hypoxemia from Methemoglobinemia

Nitric oxide combines with hemoglobin to form methemoglobin, which does not transport oxygen. Methemoglobin levels increase with the dose of INOmax; it can take 8 hours or more before steady-state methemoglobin levels are attained. Monitor methemoglobin and adjust the dose of INOmax to optimize oxygenation.

If methemoglobin levels do not resolve with decrease in dose or discontinuation of INOmax, additional therapy may be warranted to treat methemoglobinemia [see Overdosage (10)].

5.3 Airway Injury from Nitrogen Dioxide

Nitrogen dioxide (NO2) forms in gas mixtures containing NO and O2. Nitrogen dioxide may cause airway inflammation and damage to lung tissues.

If there is an unexpected change in NO2 concentration, or if the NO2 concentration reaches 3 ppm when measured in the breathing circuit, then the delivery system should be assessed in accordance with the Nitric Oxide Delivery System O&M Manual troubleshooting section, and the NO2 analyzer should be recalibrated. The dose of INOmax and/or FiO2 should be adjusted as appropriate.

5.4 Worsening Heart Failure

Patients with left ventricular dysfunction treated with INOmax may experience pulmonary edema, increased pulmonary capillary wedge pressure, worsening of left ventricular dysfunction, systemic hypotension, bradycardia and cardiac arrest. Discontinue INOmax while providing symptomatic care.

6 ADVERSE REACTIONS

The following adverse reactions are discussed elsewhere in the label;

Hypoxemia [see Warnings and Precautions (5.2)]

Worsening Heart Failure [see Warnings and Precautions (5.4)]

6.1 Clinical Trials Experience

Because clinical trials are conducted under widely varying conditions, adverse reaction rates observed in the clinical trials of a drug cannot be directly compared to rates in the clinical trials of another drug and may not reflect the rates observed in practice. The adverse reaction information from the clinical studies does, however, provide a basis for identifying the adverse events that appear to be related to drug use and for approximating rates.

Controlled studies have included 325 patients on INOmax doses of 5 to 80 ppm and 251 patients on placebo. Total mortality in the pooled trials was 11% on placebo and 9% on INOmax, a result adequate to exclude INOmax mortality being more than 40% worse than placebo.

In both the NINOS and CINRGI studies, the duration of hospitalization was similar in INOmax and placebo-treated groups.

From all controlled studies, at least 6 months of follow-up is available for 278 patients who received INOmax and 212 patients who received placebo. Among these patients, there was no evidence of an adverse effect of treatment on the need for rehospitalization, special medical services, pulmonary disease, or neurological sequelae.

In the NINOS study, treatment groups were similar with respect to the incidence and severity of intracranial hemorrhage, Grade IV hemorrhage, periventricular leukomalacia, cerebral infarction, seizures requiring anticonvulsant therapy, pulmonary hemorrhage, or gastrointestinal hemorrhage.

In CINRGI, the only adverse reaction (>2% higher incidence on INOmax than on placebo) was hypotension (14% vs. 11%).

6.2 Post-Marketing Experience

Post marketing reports of accidental exposure to nitric oxide for inhalation in hospital staff has been associated with chest discomfort, dizziness, dry throat, dyspnea, and headache.

7 DRUG INTERACTIONS

7.1 Nitric Oxide Donor Agents

Nitric oxide donor agents such as prilocaine, sodium nitroprusside and nitroglycerine may increase the risk of developing methemoglobinemia.

8 USE IN SPECIFIC POPULATIONS

8.4 Pediatric Use

The safety and efficacy of nitric oxide for inhalation has been demonstrated in term and near-term neonates with hypoxic respiratory failure associated with evidence of pulmonary hypertension [see Clinical Studies (14.1)]. Additional studies conducted in premature neonates for the prevention of bronchopulmonary dysplasia have not demonstrated substantial evidence of efficacy [see Clinical Studies (14.3)]. No information about its effectiveness in other age populations is available.

8.5 Geriatric Use

Nitric oxide is not indicated for use in the adult population.

10 OVERDOSAGE

Overdosage with INOmax is manifest by elevations in methemoglobin and pulmonary toxicities associated with inspired NO2. Elevated NO2 may cause acute lung injury. Elevations in methemoglobin reduce the oxygen delivery capacity of the circulation. In clinical studies, NO2 levels >3 ppm or methemoglobin levels >7% were treated by reducing the dose of, or discontinuing, INOmax.

Methemoglobinemia that does not resolve after reduction or discontinuation of therapy can be treated with intravenous vitamin C, intravenous methylene blue, or blood transfusion, based upon the clinical situation.

11 DESCRIPTION

INOmax (nitric oxide gas) is a drug administered by inhalation. Nitric oxide, the active substance in INOmax, is a pulmonary vasodilator. INOmax 800 ppm is a gaseous blend of nitric oxide (0.08%) and nitrogen (99.92%). INOmax 4,880™ ppm is a gaseous blend of nitric oxide (0.488%) and nitrogen (99.51%). INOmax 800 ppm is supplied in aluminum cylinders as a compressed gas under high pressure (2,000 pounds per square inch [psi]). INOmax 4,880 ppm is supplied in aluminum cylinders as a compressed gas under high pressure (3,000 psi).

The structural formula of nitric oxide (NO) is shown below:

12 CLINICAL PHARMACOLOGY

12.1 Mechanism of Action

Nitric oxide relaxes vascular smooth muscle by binding to the heme moiety of cytosolic guanylate cyclase, activating guanylate cyclase and increasing intracellular levels of cyclic guanosine 3',5'-monophosphate, which then leads to vasodilation. When inhaled, nitric oxide selectively dilates the pulmonary vasculature, and because of efficient scavenging by hemoglobin, has minimal effect on the systemic vasculature.

INOmax appears to increase the partial pressure of arterial oxygen (PaO2) by dilating pulmonary vessels in better ventilated areas of the lung, redistributing pulmonary blood flow away from lung regions with low ventilation/perfusion (V/Q) ratios toward regions with normal ratios.

12.2 Pharmacodynamics

Effects on Pulmonary Vascular Tone in PPHN

Persistent pulmonary hypertension of the newborn (PPHN) occurs as a primary developmental defect or as a condition secondary to other diseases such as meconium aspiration syndrome (MAS), pneumonia, sepsis, hyaline membrane disease, congenital diaphragmatic hernia (CDH), and pulmonary hypoplasia. In these states, pulmonary vascular resistance (PVR) is high, which results in hypoxemia secondary to right-to-left shunting of blood through the patent ductus arteriosus and foramen ovale. In neonates with PPHN, INOmax improves oxygenation (as indicated by significant increases in PaO2).

12.3 Pharmacokinetics

The pharmacokinetics of nitric oxide has been studied in adults.

Absorption and Distribution

Nitric oxide is absorbed systemically after inhalation. Most of it traverses the pulmonary capillary bed where it combines with hemoglobin that is 60% to 100% oxygen-saturated. At this level of oxygen saturation, nitric oxide combines predominantly with oxyhemoglobin to produce methemoglobin and nitrate. At low oxygen saturation, nitric oxide can combine with deoxyhemoglobin to transiently form nitrosylhemoglobin, which is converted to nitrogen oxides and methemoglobin upon exposure to oxygen. Within the pulmonary system, nitric oxide can combine with oxygen and water to produce nitrogen dioxide and nitrite, respectively, which interact with oxyhemoglobin to produce methemoglobin and nitrate. Thus, the end products of nitric oxide that enter the systemic circulation are predominantly methemoglobin and nitrate.

Metabolism

Methemoglobin disposition has been investigated as a function of time and nitric oxide exposure concentration in neonates with respiratory failure. The methemoglobin (MetHb) concentration-time profiles during the first 12 hours of exposure to 0, 5, 20, and 80 ppm INOmax are shown in Figure 1.

Figure 1: Methemoglobin Concentration-Time Profiles Neonates Inhaling 0, 5, 20 or 80 ppm INOmax

Methemoglobin concentrations increased during the first 8 hours of nitric oxide exposure. The mean methemoglobin level remained below 1% in the placebo group and in the 5 ppm and 20 ppm INOmax groups but reached approximately 5% in the 80 ppm INOmax group. Methemoglobin levels >7% were attained only in patients receiving 80 ppm, where they comprised 35% of the group. The average time to reach peak methemoglobin was 10 ± 9 (SD) hours (median, 8 hours) in these 13 patients, but one patient did not exceed 7% until 40 hours.

Elimination

Nitrate has been identified as the predominant nitric oxide metabolite excreted in the urine, accounting for >70% of the nitric oxide dose inhaled. Nitrate is cleared from the plasma by the kidney at rates approaching the rate of glomerular filtration.

13 NONCLINICAL TOXICOLOGY

13.1 Carcinogenesis, Mutagenesis, Impairment of Fertility

No evidence of a carcinogenic effect was apparent, at inhalation exposures up to the recommended dose (20 ppm), in rats for 20 hr/day for up to two years. Higher exposures have not been investigated.

Nitric oxide has demonstrated genotoxicity in Salmonella (Ames Test), human lymphocytes, and after in vivo exposure in rats. There are no animal or human studies to evaluate nitric oxide for effects on fertility.

14 CLINICAL STUDIES

14.1 Treatment of Hypoxic Respiratory Failure (HRF)

The efficacy of INOmax has been investigated in term and near-term newborns with hypoxic respiratory failure resulting from a variety of etiologies. Inhalation of INOmax reduces the oxygenation index (OI= mean airway pressure in cm H2O × fraction of inspired oxygen concentration [FiO2]× 100 divided by systemic arterial concentration in mm Hg [PaO2]) and increases PaO2 [see Clinical Pharmacology (12.1)].

NINOS Study

The Neonatal Inhaled Nitric Oxide Study (NINOS) was a double-blind, randomized, placebo-controlled, multicenter trial in 235 neonates with hypoxic respiratory failure. The objective of the study was to determine whether inhaled nitric oxide would reduce the occurrence of death and/or initiation of extracorporeal membrane oxygenation (ECMO) in a prospectively defined cohort of term or near-term neonates with hypoxic respiratory failure unresponsive to conventional therapy. Hypoxic respiratory failure was caused by meconium aspiration syndrome (MAS; 49%), pneumonia/sepsis (21%), idiopathic primary pulmonary hypertension of the newborn (PPHN; 17%), or respiratory distress syndrome (RDS; 11%). Infants ≤14 days of age (mean, 1.7 days) with a mean PaO2 of 46 mm Hg and a mean oxygenation index (OI) of 43 cm H2O / mm Hg were initially randomized to receive 100% O2 with (n=114) or without (n=121) 20 ppm nitric oxide for up to 14 days. Response to study drug was defined as a change from baseline in PaO2 30 minutes after starting treatment (full response = >20 mm Hg, partial = 10–20 mm Hg, no response = <10 mm Hg). Neonates with a less than full response were evaluated for a response to 80 ppm nitric oxide or control gas. The primary results from the NINOS study are presented in Table 1.

Table 1: Summary of Clinical Results from NINOS Study
 | Control (n=121) | NO (n=114) | P value
Death or ECMO [Extracorporeal membrane oxygenation] , [Death or need for ECMO was the study's primary end point] | 77 (64%) | 52 (46%) | 0.006
Death | 20 (17%) | 16 (14%) | 0.60
ECMO | 66 (55%) | 44 (39%) | 0.014

Although the incidence of death by 120 days of age was similar in both groups (NO, 14%; control, 17%), significantly fewer infants in the nitric oxide group required ECMO compared with controls (39% vs. 55%, p = 0.014). The combined incidence of death and/or initiation of ECMO showed a significant advantage for the nitric oxide treated group (46% vs. 64%, p = 0.006). The nitric oxide group also had significantly greater increases in PaO2 and greater decreases in the OI and the alveolar-arterial oxygen gradient than the control group (p<0.001 for all parameters). Significantly more patients had at least a partial response to the initial administration of study drug in the nitric oxide group (66%) than the control group (26%, p<0.001). Of the 125 infants who did not respond to 20 ppm nitric oxide or control, similar percentages of NO-treated (18%) and control (20%) patients had at least a partial response to 80 ppm nitric oxide for inhalation or control drug, suggesting a lack of additional benefit for the higher dose of nitric oxide. No infant had study drug discontinued for toxicity. Inhaled nitric oxide had no detectable effect on mortality. The adverse events collected in the NINOS trial occurred at similar incidence rates in both treatment groups [see Adverse Reactions (6.1)]. Follow-up exams were performed at 18–24 months for the infants enrolled in this trial. In the infants with available follow-up, the two treatment groups were similar with respect to their mental, motor, audiologic, or neurologic evaluations.

CINRGI Study

This study was a double-blind, randomized, placebo-controlled, multicenter trial of 186 term and near-term neonates with pulmonary hypertension and hypoxic respiratory failure. The primary objective of the study was to determine whether INOmax would reduce the receipt of ECMO in these patients. Hypoxic respiratory failure was caused by MAS (35%), idiopathic PPHN (30%), pneumonia/sepsis (24%), or RDS (8%). Patients with a mean PaO2 of 54 mm Hg and a mean OI of 44 cm H2O / mm Hg were randomly assigned to receive either 20 ppm INOmax (n=97) or nitrogen gas (placebo; n=89) in addition to their ventilatory support. Patients who exhibited a PaO2 >60 mm Hg and a pH < 7.55 were weaned to 5 ppm INOmax or placebo. The primary results from the CINRGI study are presented in Table 2.

Table 2: Summary of Clinical Results from CINRGI Study
 | Placebo | INOmax | P value
ECMO [Extracorporeal membrane oxygenation] , [ECMO was the primary end point of this study] | 51/89 (57%) | 30/97 (31%) | <0.001
Death | 5/89 (6%) | 3/97 (3%) | 0.48

Significantly fewer neonates in the INOmax group required ECMO compared to the control group (31% vs. 57%, p<0.001). While the number of deaths were similar in both groups (INOmax, 3%; placebo, 6%), the combined incidence of death and/or receipt of ECMO was decreased in the INOmax group (33% vs. 58%, p<0.001).

In addition, the INOmax group had significantly improved oxygenation as measured by PaO2, OI, and alveolar-arterial gradient (p<0.001 for all parameters). Of the 97 patients treated with INOmax, 2 (2%) were withdrawn from study drug due to methemoglobin levels >4%. The frequency and number of adverse events reported were similar in the two study groups [see Adverse Reactions (6.1)].

In clinical trials, reduction in the need for ECMO has not been demonstrated with the use of inhaled nitric oxide in neonates with congenital diaphragmatic hernia (CDH).

14.2 Ineffective in Adult Respiratory Distress Syndrome (ARDS)

In a randomized, double-blind, parallel, multicenter study, 385 patients with adult respiratory distress syndrome (ARDS) associated with pneumonia (46%), surgery (33%), multiple trauma (26%), aspiration (23%), pulmonary contusion (18%), and other causes, with PaO2/FiO2 <250 mm Hg despite optimal oxygenation and ventilation, received placebo (n=193) or INOmax (n=192), 5 ppm, for 4 hours to 28 days or until weaned because of improvements in oxygenation. Despite acute improvements in oxygenation, there was no effect of INOmax on the primary endpoint of days alive and off ventilator support. These results were consistent with outcome data from a smaller dose ranging study of nitric oxide (1.25 to 80 ppm). INOmax is not indicated for use in ARDS.

14.3 Ineffective in Prevention of Bronchopulmonary Dysplasia (BPD)

The safety and efficacy of INOmax for the prevention of chronic lung disease [bronchopulmonary dysplasia, (BPD)] in neonates ≤ 34 weeks gestational age requiring respiratory support has been studied in four large, multi-center, double-blind, placebo-controlled clinical trials in a total of 2,600 preterm infants. Of these, 1,290 received placebo, and 1,310 received inhaled nitric oxide at doses ranging from 5-20 ppm, for treatment periods of 7-24 days duration. The primary endpoint for these studies was alive and without BPD at 36 weeks postmenstrual age (PMA). The need for supplemental oxygen at 36 weeks PMA served as a surrogate endpoint for the presence of BPD. Overall, efficacy for the prevention of bronchopulmonary dysplasia in preterm infants was not established. There were no meaningful differences between treatment groups with regard to overall deaths, methemoglobin levels, or adverse events commonly observed in premature infants, including intraventricular hemorrhage, patent ductus arteriosus, pulmonary hemorrhage, and retinopathy of prematurity.

The use of INOmax for prevention of BPD in preterm neonates ≤ 34 weeks gestational age is not recommended.

16 HOW SUPPLIED/STORAGE AND HANDLING

INOmax (nitric oxide) is available in the following sizes:

Size D | Portable aluminum cylinders containing 353 liters at STP of nitric oxide gas in 800 ppm concentration in nitrogen (delivered volume 344 liters) (NDC 64693-002-01)
Size 88 | Aluminum cylinders containing 1963 liters at STP of nitric oxide gas in 800 ppm concentration in nitrogen (delivered volume 1918 liters) (NDC 64693-002-02)
0.4 liter | Portable aluminum cylinders containing 78 liters at STP of nitric oxide gas in 4,880 ppm concentration in nitrogen (delivered volume 70 liters) (NDC 64693-003-01)

STORAGE AND HANDLING

Store at 25°C (77°F) with excursions permitted between 15° to 30°C (59° to 86°F) [see USP Controlled Room Temperature].

All regulations concerning handling of pressure vessels must be followed.

Protect the cylinders from shocks, falls, oxidizing and flammable materials, moisture, and sources of heat or ignition.

INOmax MR conditional labeled cylinders (i.e., size 88 aluminum cylinder) may be used at 100 gauss or less. Use of any other cylinders (e.g., size D or 0.4 liter aluminum cylinder) may create a projectile hazard.

Occupational Exposure

The exposure limit set by the Occupational Safety and Health Administration (OSHA) for nitric oxide is 25 ppm, and for NO2 the limit is 5 ppm.

For a list of patents, see https://www.mallinckrodt.com/patents/

Distributed by

INO Therapeutics LLC
Bridgewater, NJ 08807, USA
© 2023 Mallinckrodt

PRINCIPAL DISPLAY PANEL - 1963 Liter Cylinder Label

Rx only

INOmax®
nitric oxide
FOR
INHALATION

800 PPM

CAUTION: HIGH PRESSURE GAS. CAN CAUSE RAPID SUFFOCATION WITHOUT WARNING. Use equipment rated
for cylinder pressure. Store and use with adequate ventilation. Secure cylinder in use and storage. Close valve
after each use and when empty. USE IN ACCORDANCE WITH APPROPRIATE SDS.

WARNING: Administration of this gas mixture may be hazardous or contraindicated. For use only by or under
the supervision of a licensed practitioner who is experienced in the use and administration of gas mixtures, and
is familiar with the indications, effects, dosages, methods, and frequency and duration of administration, and
with the hazards, contraindications and side effects and the precautions to be taken.

FIRST AID: IF INHALED, remove person to fresh air. If not breathing, give artificial respiration. If breathing is
difficult, give oxygen. Get medical help.

RETURN WITH 25 PSIG.
TO BE REFILLED ONLY BY A PHARMACEUTICAL FACILITY AUTHORIZED BY INO Therapeutics LLC

Manufactured Under Pharmaceutical Current Good Manufacturing Practices (cGMPs).
DO NOT REMOVE THIS PRODUCT LABEL.

Store at 25°C (77°F)
[see USP Controlled Room Temperature].

Volume 1963 Liters

Mallinckrodt™
Pharmaceuticals

Manufactured by:
Mallinckrodt Manufacturing LLC
1060 Allendale Dr.
Port Allen, LA 70767 USA
For Product Inquiry 1-877-KNOW INO
(566-9466)

UN 1956
Compressed Gas, N.O.S.
(Nitric Oxide, Nitrogen)
2.2
Net Weight: 2.5 Kg

NDC 64693-002-02

MADE IN USA

Label No. SPC-LBL-0060 R8

PRINCIPAL DISPLAY PANEL - 78 Liter Cylinder Label

INOmax®
nitric oxide
FOR INHALATION
4,880 PPM

2

Rx only

CAUTION: HIGH PRESSURE GAS. CAN CAUSE
RAPID SUFFOCATION WITHOUT WARNING.
Use equipment rated for cylinder pressure.
Store and use with adequate ventilation.
Secure cylinder in use and storage. USE IN
ACCORDANCE WITH APPROPRIATE SDS.

WARNING: Administration of this gas mixture
may be hazardous or contraindicated. For use
only by or under the supervision of a licensed
practitioner who is experienced in the use and
administration of gas mixtures, and is familiar
with the indications, effects, dosages, methods,
and frequency and duration of administration, and
with the hazards, contraindications and side effects
and the precautions to be taken.

FIRST AID: IF INHALED,
remove person to fresh air. If
not breathing, give artificial
respiration. If breathing is
difficult, give oxygen.
Get medical help.

Manufactured Under Pharmaceutical
Current Good Manufacturing Practices (cGMPs).
Manufactured by: Mallinckrodt Manufacturing LLC
1060 Allendale Dr., Port Allen, LA 70767 USA
For Product Inquiry 1-877-KNOW INO (566-9466)

Recommended Dosage: See prescribing information.

Storage: Store at 25°C (77°F) [see USP Controlled Room Temperature].

Net Weight: 0.1 Kg Volume: 78 Liters

DO NOT REMOVE THIS PRODUCT LABEL.

Mallinckrodt™
Pharmaceuticals

NDC 64693-003-01

UN 1956
Compressed Gas, N.O.S.
(Nitric Oxide, Nitrogen) 2.2

MADE IN USA

To be refilled only by a pharmaceutical facility authorized by INO Therapeutics LLC

SPC-LBL-0900 R1

do not discard